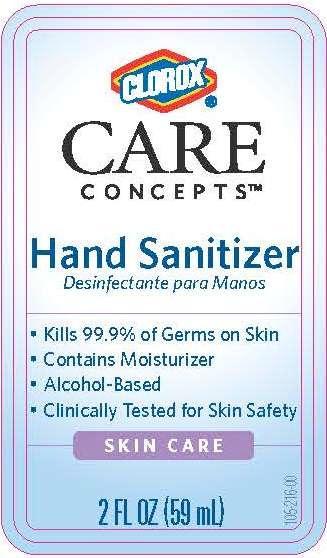 DRUG LABEL: Clorox Care Concepts Hand Sanitizer
NDC: 26509-0002 | Form: SOLUTION
Manufacturer: The Clorox Company
Category: otc | Type: HUMAN OTC DRUG LABEL
Date: 20140414

ACTIVE INGREDIENTS: ALCOHOL 67 mL/100 mL
INACTIVE INGREDIENTS: WATER; ISOPROPYL ALCOHOL; GLYCERIN; GLYCERYL LAURATE

Drug Facts

Active ingredient

Alcohol 67 percent

Purpose

Antiseptic

Use

Hand sanitizer to decrease bacteria on the skin that potentially can cause disease

Warnings

Flammable. Keep away from fire or flame.

For external use only.

When using this product, do not use in the eyes.

Discontinue use and ask a doctor if

- irritate and redness develop.
- condition persists for more than 72 hours.

Keep out of reach of children.

If swallowed, get medical help or contact a Poison Control Center immediately.

Directions

Wet hands thoroughly with product and allow to dry without wiping.

Other Information

Store in a cool, dry place below 104 deg F (40 deg C).

Inactive ingredients

Water, Isopropyl Alcohol, Glycerin, Glyceryl Laurate.

PACKAGE LABEL

Clorox Care Concepts

Hand Sanitizer